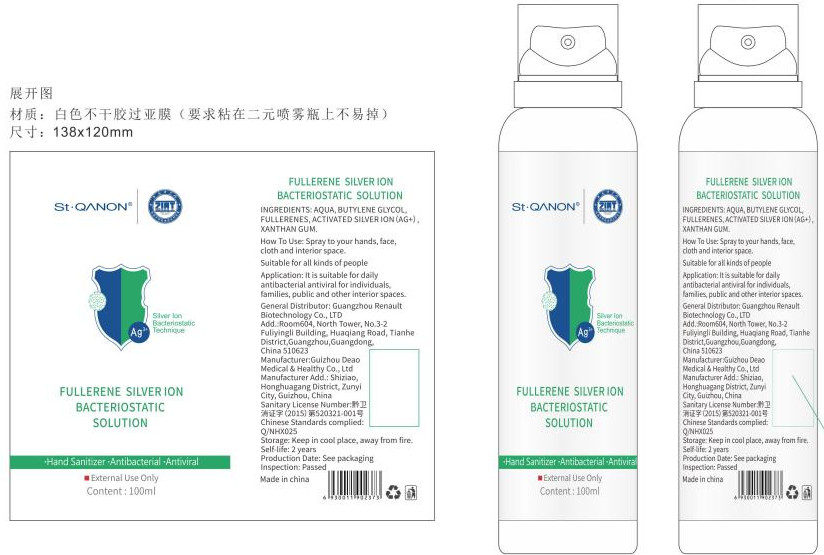 DRUG LABEL: fullerene silver ion bacteriostatic solution
NDC: 54760-001 | Form: LIQUID
Manufacturer: GUANGZHOU RENAULT BIOTECHNOLOGY CO., LTD.
Category: otc | Type: HUMAN OTC DRUG LABEL
Date: 20200417

ACTIVE INGREDIENTS: SILVER OXIDE 0.06 mg/100 mL
INACTIVE INGREDIENTS: XANTHAN GUM; BUTYLENE GLYCOL; BUCKMINSTERFULLERENE

DOSAGE AND ADMINISTRATION

Keep away from sun light

INACTIVE INGREDIENT

BUTYLENE GLYCOL

FULLERENES

XANTHAN GUM

INDICATIONS AND USAGE

Spray to your hands, face,cloth and interior space.Sultable for all kinds of peoplepplcation: It is suitable for daily

ACTIVE INGREDIENT

ACTIVATED SILVER ION(AG+)

keep out of children

PURPOSE

Disinfection
Sterilization

WARNINGS

Away from fire.